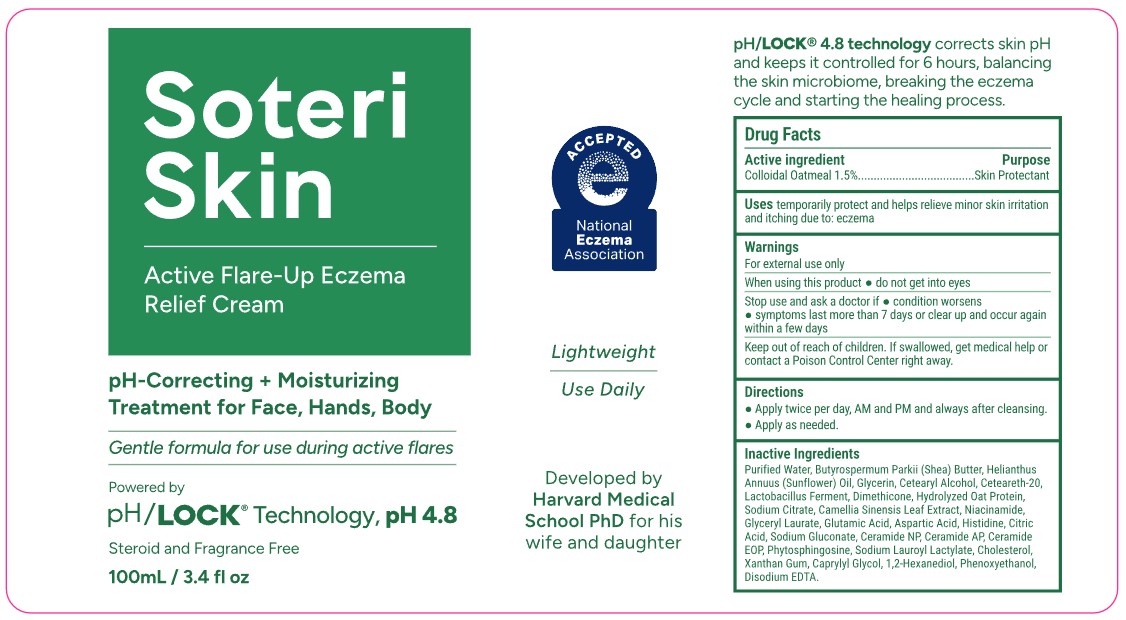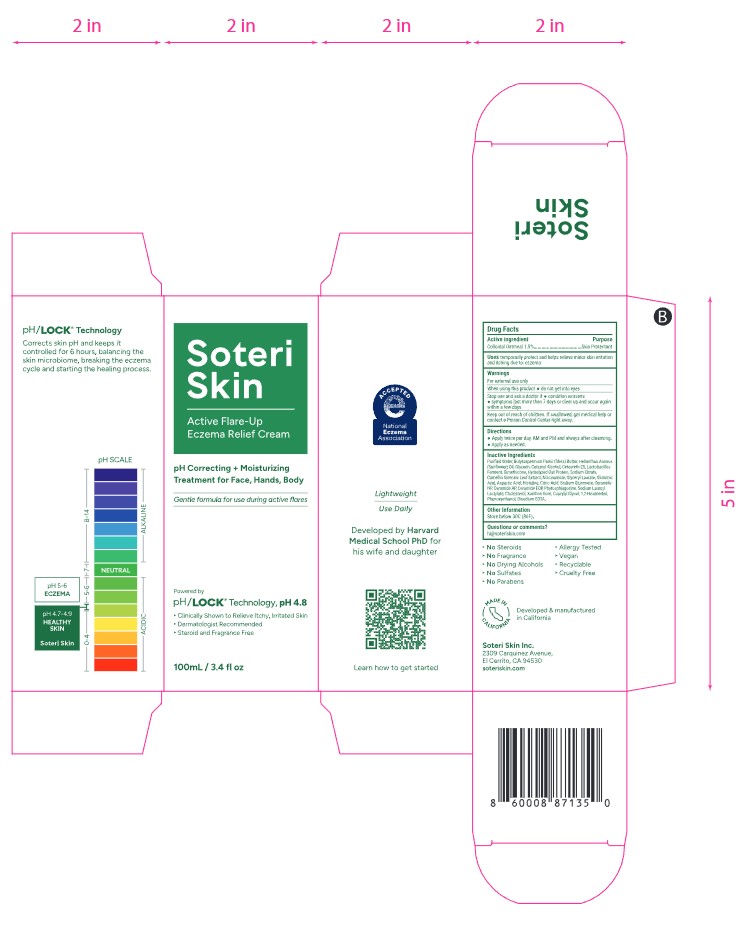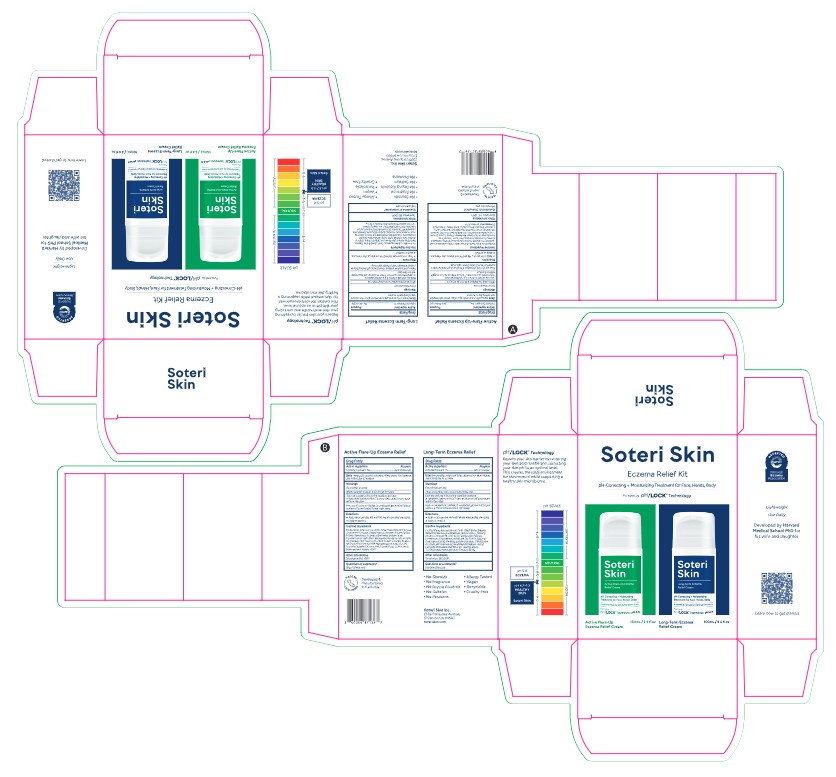 DRUG LABEL: Soteri Skin Active Flare-Up Eczema Relief Cream
NDC: 85265-102 | Form: EMULSION
Manufacturer: Soteri Skin, Inc.
Category: otc | Type: HUMAN OTC DRUG LABEL
Date: 20251210

ACTIVE INGREDIENTS: OATMEAL 1.5 g/100 mL
INACTIVE INGREDIENTS: AQUA; HELIANTHUS ANNUUS (SUNFLOWER) SEED OIL; CETEARETH-20; OAT AMINO ACIDS; LACTOBACILLUS; DIMETHICONE; CETEARYL ALCOHOL; NIACINAMIDE; GLYCERYL LAURATE; GLUTAMIC ACID; SODIUM CITRATE; ANHYDROUS CITRIC ACID; XANTHAN GUM; PHENOXYETHANOL; BUTYROSPERMUM PARKII (SHEA) BUTTER; GLYCERIN; CAMELLIA SINENSIS LEAF; CAPRYLYL GLYCOL; HISTIDINE; PHYTOSPHINGOSINE; SODIUM LAUROYL LACTYLATE; CHOLESTEROL; 1,2-HEXANEDIOL; EDETATE DISODIUM; CERAMIDE AP; ASPARTIC ACID; SODIUM GLUCONATE; CERAMIDE NP; CERAMIDE 1

Soteri Skin Active Flare-Up Eczema Relief Cream 100 mL / 3.4 fl oz (NDC 85265-102-01)

Active Ingredient

Colloidal Oatmeal 1.5%

Purpose

Skin Protectant

Uses

temporarily protect and helps relieve minor skin irritation and itching due to: eczema

Warnings

For external use only

When using this product

- do not get into eyes

Stop use and ask doctor if

- condition worsens
- symptoms last more than 7 days or clear up and occur again within a few days

Keep out of reach of children. If swallowed, get medical help or contact a Poison Control Center right away.

Directions

- Apply twice per day, AM and PM and always after cleansing.
- Apply as needed.

Inactive Ingredients

Purified Water, Butyrospermum Parkii (Shea) Butter, Helianthus Annuus (Sunflower) Oil, Glycerin, Cetearyl Alcohol, Ceteareth-20, Lactobacillus Ferment, Dimethicone, Hydrolyzed Oat Protein, Sodium Citrate, Camellia Sinensis Leaf Extract, Niacinamide, Glyceryl Laurate, Glutamic Acid, Aspartic Acid, Histidine, Citric Acid, Sodium Gluconate, Ceramide NP, Ceramide AP, Ceramide EOP, Phytosphingosine, Sodium Lauroyl Lactylate, Cholesterol, Xanthan Gum, Caprylyl Glycol, 1,2-Hexanediol, Phenoxyethanol, Disodium EDTA.

Other Information

Store below 30C (86F)